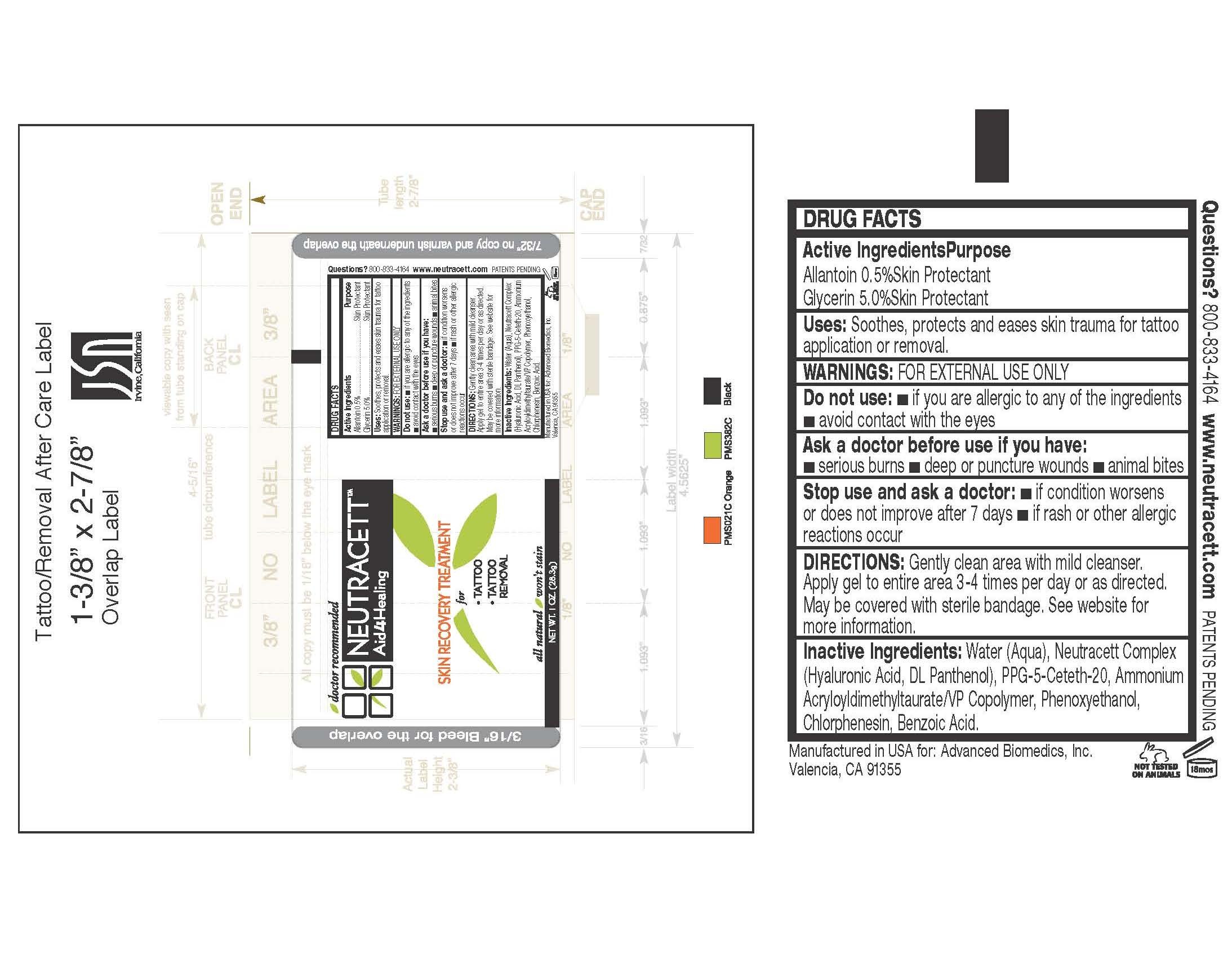 DRUG LABEL: NEUTRACETT
NDC: 51435-002 | Form: GEL
Manufacturer: ADVANCED BIOMEDICS INC
Category: otc | Type: HUMAN OTC DRUG LABEL
Date: 20100810

ACTIVE INGREDIENTS: ALLANTOIN 0.5 mg/0.1 g; GLYCERIN 50 mg/1 g
INACTIVE INGREDIENTS: WATER; HYALURONIC ACID; PANTHENOL; PPG-5-CETETH-20; PHENOXYETHANOL; CHLORPHENESIN; BENZOIC ACID

TUBE LABEL

INACTIVE INGREDIENT

Inactive Ingredients: Water (Aqua), Neutracett Complex (Hyaluronic Acid, DL Panthenol), PPG-5-Ceteth-20, Ammonium Acryloyldimethyltaurate/VP Copolymer, Phenoxyethanol, Chlorphenesin, Benzoic Acid.

Active ingredients/Purpose

Allantoin 0.5% Skin Protectant

Glycerin 5.0% Skin Protectant

Ask a doctor before use if you have: *serious burns * deep or puncture wounds * animal bites

Questions? 800-833-4164

www.neutracett.com Patents Pending

Do not use: *if you are allergic to any of the ingredients *avoid contact with the eyes

Stop use and ask a doctor: * if condition worsens or does not improve after 7 days * if rash or other allergic reactions occur

PURPOSE

Uses: Soothes, protects and eases skin trauma for tattoo application or removal.

Warnings: For external use only.

DOSAGE AND ADMINISTRATION

Directions: Gently clean area with mild cleanser. Apply gel to entire area 3-4 times per day or as directed. May be covered with sterile bandage. See website for more information.

PACKAGE LABEL

Neutracett

Aid 4-Healing

Skin Recovery Treatment

For Tattoo, tattoo removal

All natural / won’t stain